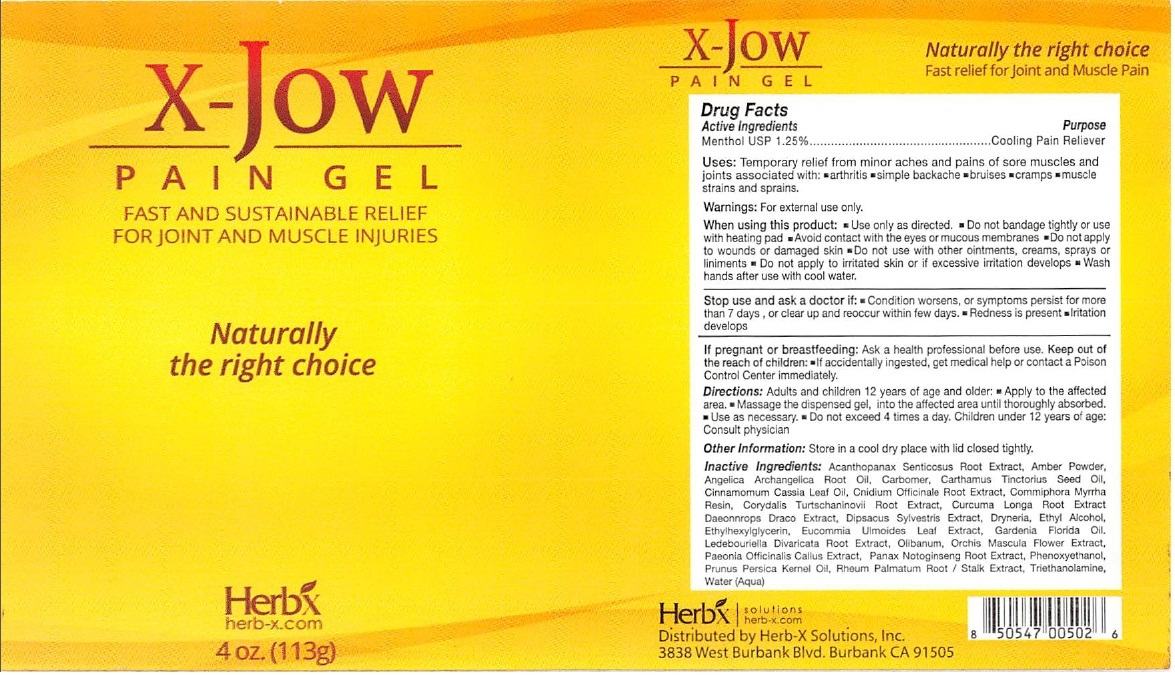 DRUG LABEL: XJOW
NDC: 69934-001 | Form: GEL
Manufacturer: Omom Pharmaceuticals, Inc.
Category: otc | Type: HUMAN OTC DRUG LABEL
Date: 20170130

ACTIVE INGREDIENTS: MENTHOL, UNSPECIFIED FORM 1.25 g/100 g
INACTIVE INGREDIENTS: ELEUTHERO; AMBER; ANGELICA ROOT OIL; CARBOXYPOLYMETHYLENE; SAFFLOWER OIL; CHINESE CINNAMON LEAF OIL; CNIDIUM OFFICINALE ROOT; MYRRH; CORYDALIS YANHUSUO TUBER; TURMERIC; DAEMONOROPS DRACO RESIN; DIPSACUS FULLONUM ROOT; DRYNARIA FORTUNEI ROOT; ALCOHOL; ETHYLHEXYLGLYCERIN; EUCOMMIA ULMOIDES LEAF; GARDENIA JASMINOIDES FRUIT; SAPOSHNIKOVIA DIVARICATA ROOT; FRANKINCENSE; ORCHIS MASCULA FLOWER; PAEONIA OFFICINALIS ROOT; PANAX NOTOGINSENG ROOT; PHENOXYETHANOL; PRUNUS PERSICA SEED; RHEUM PALMATUM ROOT; TROLAMINE; WATER

XJOW PAIN GEL

Active Ingredients

Menthol USP 1.25%

Purpose

Cooling Pain Reliever

INDICATIONS AND USAGE

Uses: Temporary relief from minor aches and pains of sore muscles and joints associated with: • arthritis • simple backache • bruises • cramps • muscle strains and sprains.

Warnings: For external use only.

When using this product: • Use only as directed. • Do not bandage tightly or use with heating pad • Avoid contact with the eyes or mucous membranes • Do not apply to wounds or damaged skin • Do not use with other ointments, creams, sprays or liniments • Do not apply to irritated skin or if excessive irritation develops • Wash hands after use with cool water.

Stop use and ask a doctor if: • Condition worsens, or symptoms persist for more than 7 days, or clear up and reoccur within few days. • Redness is present • Irritation develops

If pregnant or breastfeeding: Ask a health professional before use.

KEEP OUT OF REACH OF CHILDREN

Keep out of the reach of children: • If accidentally ingested, get medial help or contact a Poison Control Center immediately.

DOSAGE AND ADMINISTRATION

Directions: Adults and children 12 years of age and older: • Apply to the affected area. • Massage the dispensed gel, into the affected area until thoroughly absorbed. • Use as necessary. • Do not exceed 4 times a day. Children under 12 years of age: Consult physician

INACTIVE INGREDIENT

Inactive Ingredients: Acanthopanax Senticosus Root Extract, Amber Powder, Angelica Archangelica Root Oil, Carbomer, Carthamus Tinctorius Seed Oil, Cinnamomum Cassia Leaf Oil, Cnidium Officinale Root Extract, Commiphora Myrrha Resin, Corydalis Turtschaninovii Root Extract, Curcuma Longa Root Extract, Daeonnrops Draco Extract, Dipsacus Sylvestris Extract, Dryneria, Ethyl Alcohol, Ethylhexylglycerin, Eucommia Ulmoides Leaf Extract, Gardenia Florida Oil, Ledebouriella Divaricata Root Extract, Olibanum, Orchis Mascula Flower Extract, Paeonia Officinalis Callus Extract, Panax Notoginseng Root Extract, Phenoxyethanol, Prunus Persica Kernel Oil, Rheum Palmatum Root / Stalk Extract, Triethanolamine, Water (Aqua)

Other information: Store in a cool dry place with lid closed tightly.

FAST AND SUSTAINABLE RELIEF

FOR JOINT AND MUSCLE INJURIES

Naturally the right choice

Distributed by Herb-X Solutions, Inc.

3838 West Burbank Blvd. Burbank CA 91505